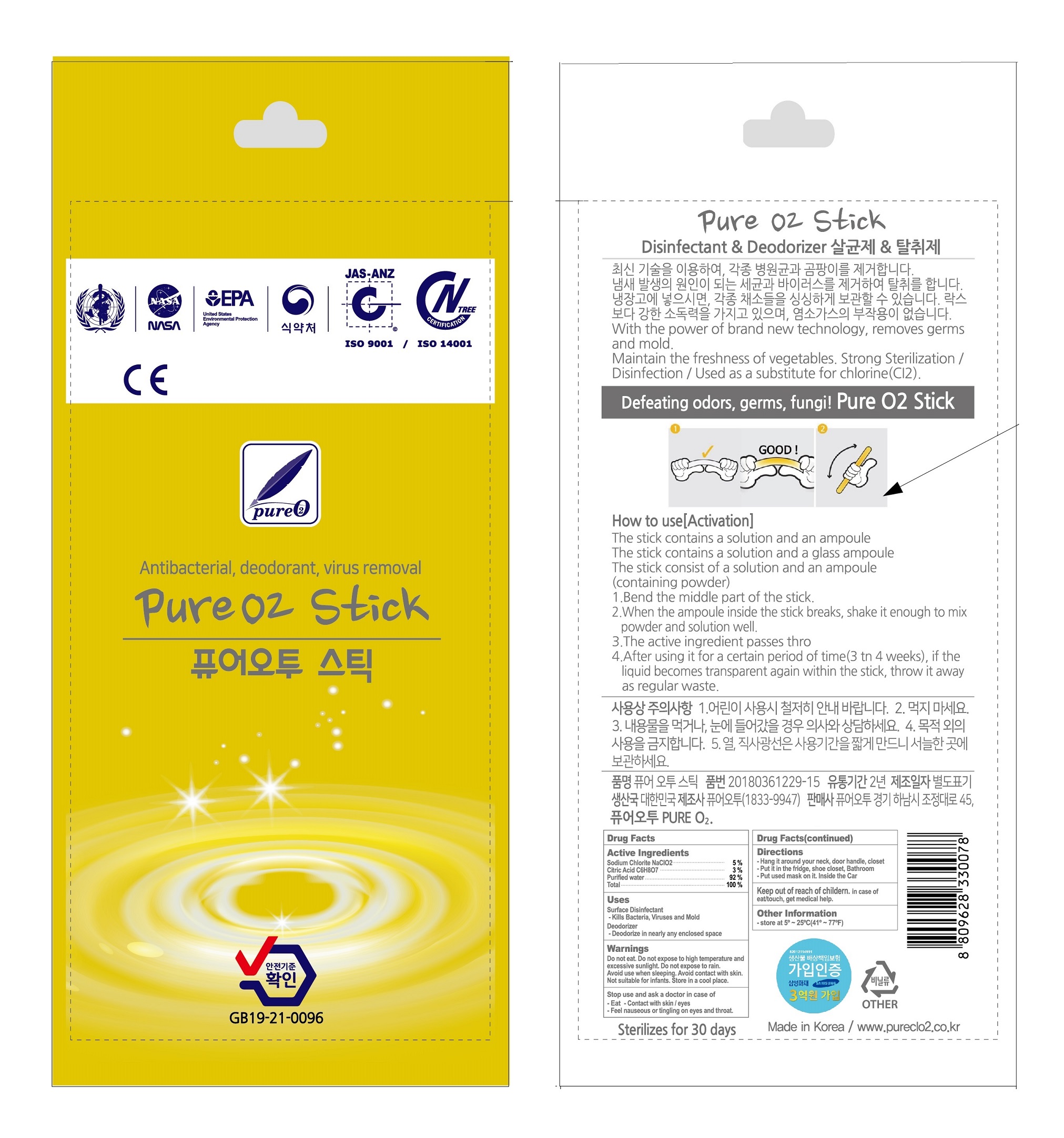 DRUG LABEL: PURE O2STICK
NDC: 75124-0003 | Form: LIQUID
Manufacturer: Pure O2
Category: otc | Type: HUMAN OTC DRUG LABEL
Date: 20231116

ACTIVE INGREDIENTS: SODIUM CHLORITE 5 g/100 g
INACTIVE INGREDIENTS: CITRIC ACID MONOHYDRATE; WATER

Drug Facts

ACTIVE INGREDIENT

sodium chlorite

INACTIVE INGREDIENT

citric acid, water

PURPOSE

anti bacteria, deodorization, disinfectant

KEEP OUT OF REACH OF THE CHILDREN

INDICATIONS AND USAGE

please see the label attached

WARNINGS

■ For external use only.

■ Do not use in eyes.

■ lf swallowed, get medical help promptly.

■ Stop use, ask doctor lf irritation occurs.

■ Keep out of reach of children.

DOSAGE AND ADMINISTRATION

for external use only